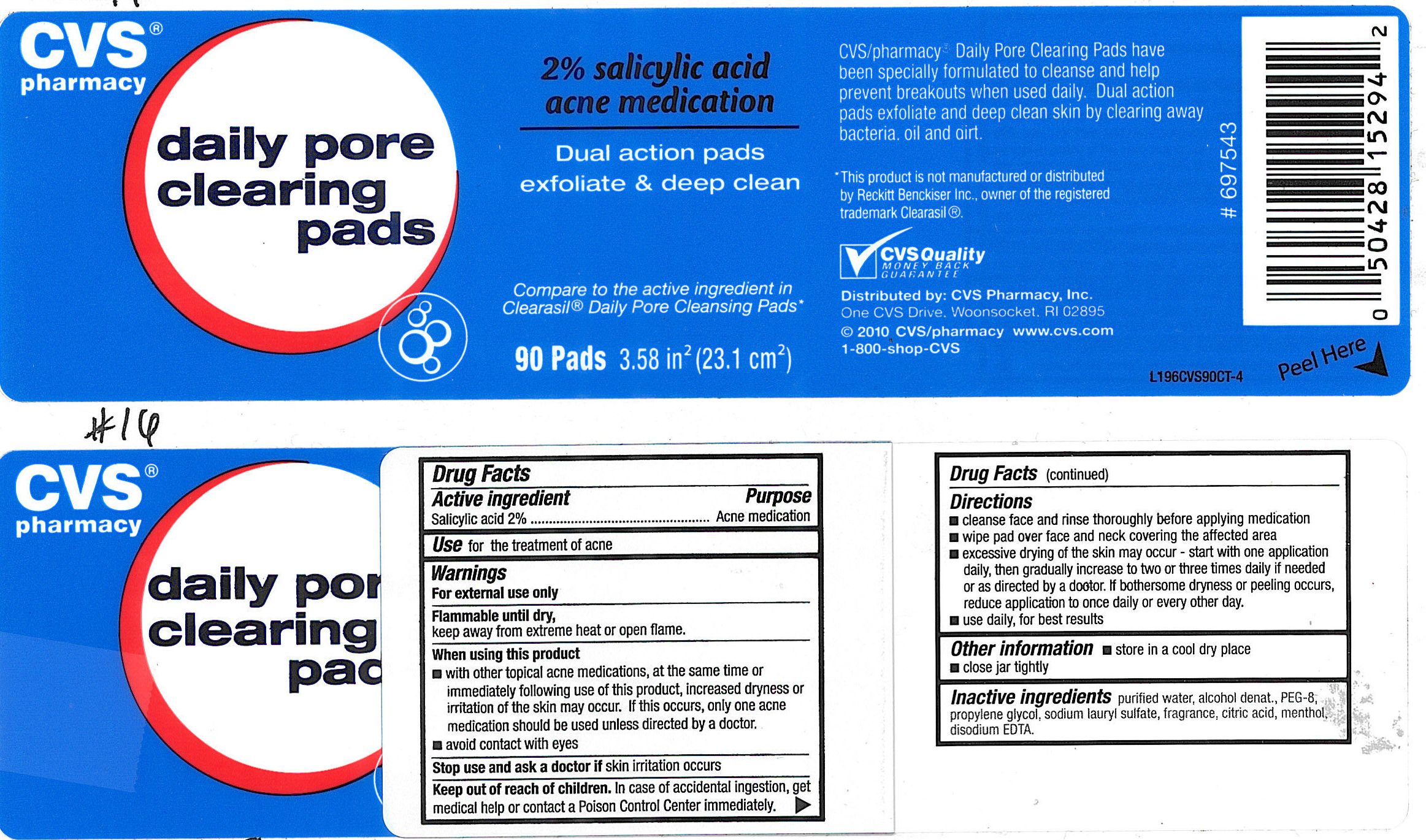 DRUG LABEL: CVS Daily Pore Clearing Pads
NDC: 59779-077 | Form: SWAB
Manufacturer: CVS PHARMACY
Category: otc | Type: HUMAN OTC DRUG LABEL
Date: 20100713

ACTIVE INGREDIENTS: SALICYLIC ACID 21 mg/1 1
INACTIVE INGREDIENTS: WATER; DOCUSATE SODIUM; CARBOMER HOMOPOLYMER TYPE C; SODIUM HYDROXIDE; EDETATE SODIUM

drug facts

Active ingredient Purpose
Salicylic Acid, 2%.......................................Acne medication

Use
- for the treatment of acne

Keep out of reach of children.If swallowed, get medical help or contact a Poison
Control Center immediately.

Directions

- cleanse face and rinse thoroughly before applying medication
- wipe pad over face and neck covering the affected area
- excessive drying of the skin may occur - start with one application daily,
then gradually increase to two or three times daily if needed or as directed by a doctor.
If bothersome dryness or peeling occurs, reduce application to once a day or every other day.
- use daily for best results
Other Information
- store in a cool dry place
- close jar tightly

Warnings
For external use only.
Flammable until dry,
keep away from extreme heat or open flame.
When using this product
- with other topical acne medications, at the same time or immediately following use of this product, increased dryness or irritation may occur.
If this occurs, only one acne medication should be used unless directed by a doctor
- avoid contact with eyes
Stop use and ask a doctor if skin irritation occurs
Keep out of reach of children. If swallowed, get medical help or contact a Poison
Control Center immediately.

Directions

- cleanse face and rinse thoroughly before applying medication
- wipe pad over face and neck covering the affected area
- excessive drying of the skin may occur - start with one application daily,
then gradually increase to two or three times daily if needed or as directed by a doctor.
If bothersome dryness or peeling occurs, reduce application to once a day or every other day.
- use daily for best results
Other Information
- store in a cool dry place
- close jar tightly

INACTIVE INGREDIENT

Inactive Ingredients purified water, alcohol denat., PEG-8, propylene glycol,
sodium lauryl sulfate, fragrance, citric acid, menthol, disodium EDTA.